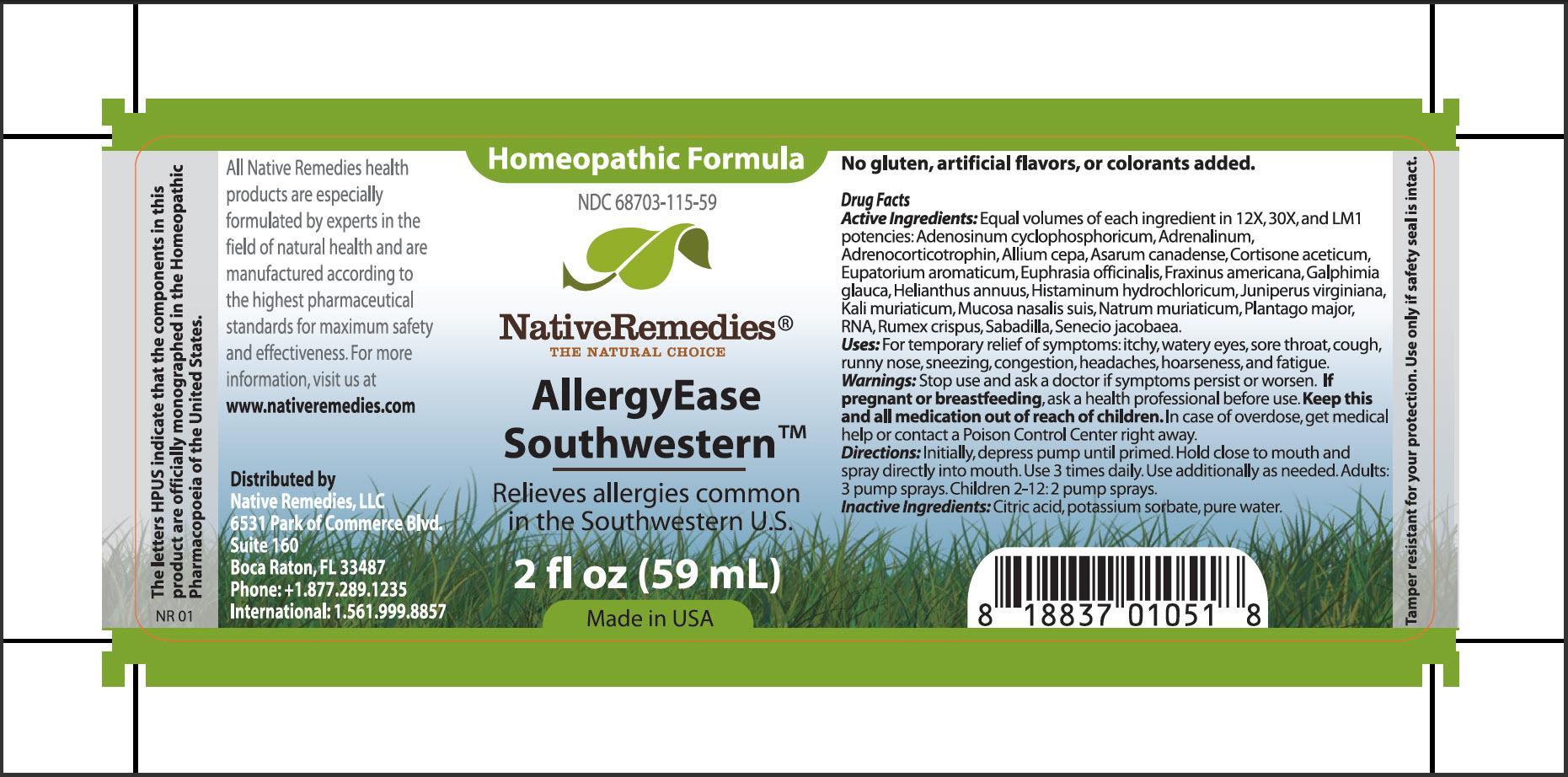 DRUG LABEL: AllergyEase Southwestern
NDC: 68703-115 | Form: SPRAY
Manufacturer: Native Remedies, LLC
Category: homeopathic | Type: HUMAN OTC DRUG LABEL
Date: 20130702

ACTIVE INGREDIENTS: ADENOSINE CYCLIC PHOSPHATE 12 [hp_X]/59 mL; EPINEPHRINE 12 [hp_X]/59 mL; CORTICOTROPIN 12 [hp_X]/59 mL; ONION 12 [hp_X]/59 mL; ASARUM CANADENSE ROOT 12 [hp_X]/59 mL; CORTISONE ACETATE  12 [hp_X]/59 mL; AGERATINA AROMATICA ROOT 12 [hp_X]/59 mL; EUPHRASIA STRICTA 12 [hp_X]/59 mL; FRAXINUS AMERICANA BARK 12 [hp_X]/59 mL; GALPHIMIA GLAUCA FLOWERING TOP 12 [hp_X]/59 mL; HELIANTHUS ANNUUS FLOWERING TOP 12 [hp_X]/59 mL; HISTAMINE DIHYDROCHLORIDE 12 [hp_X]/59 mL; JUNIPERUS VIRGINIANA TWIG 12 [hp_X]/59 mL; POTASSIUM CHLORIDE 12 [hp_X]/59 mL; SUS SCROFA NASAL MUCOSA 12 [hp_X]/59 mL; SODIUM CHLORIDE 12 [hp_X]/59 mL; PLANTAGO MAJOR 12 [hp_X]/59 mL; SACCHAROMYCES CEREVISIAE RNA 12 [hp_X]/59 mL; RUMEX CRISPUS ROOT 12 [hp_X]/59 mL; SCHOENOCAULON OFFICINALE SEED 12 [hp_X]/59 mL; JACOBAEA VULGARIS 12 [hp_X]/59 mL
INACTIVE INGREDIENTS: CITRIC ACID MONOHYDRATE; POTASSIUM SORBATE; WATER

AllergyEase Southwestern

PURPOSE

Relieves allergies common in the Southwestern U.S.

Drug Facts
Active Ingredients: Equal volumes of each ingredient in 12X, 30X, and LM1 potencies: Adenosinum cyclophosphoricum, Adrenalinum, Adrenocorticotrophin, Allium cepa, Asarum canadense, Cortisone aceticum, Eupatorium aromaticum, Euphrasia officinalis, Fraxinus americana, Galphimia glauca, Helianthus annus, Histaminum hydrochloricum, Juniperus virginiana, Kali muriaticum, Mucosa nasalis suis, Natrum muriaticum, Plantago major, RNA, Rumex crispus, Sabadilla, Senecio jacobaea

INDICATIONS AND USAGE

Uses: For temporary relief of symptoms: itchy, watery eyes, sore throat, cough, runny nose, sneezing, congestion, headaches, hoarseness, and fatigue

WARNINGS

Warnings: Stop use and ask a doctor if symptoms persist or worsen

PREGNANCY OR BREAST FEEDING

If pregnant or breastfeeding, ask a health professional before use

KEEP OUT OF REACH OF CHILDREN

Keep this and all medications out of reach of children

OVERDOSAGE

In case of overdose, get medical help or contact a Poison Control Center righ away

DOSAGE AND ADMINISTRATION

Directions: Initially, depress pump until primed. Hold close to mouth and spray directly into mouth. Use 3 times daily. Use additionally as needed. Adults: 3 pump sprays. Children 2-12: 2 pump sprays

Inactive Ingredients: Citric acid, potassium sorbate, pure water

PATIENT COUNSELING INFORMATION

The letter HPUS indicate that the components in this product are officially monographed in the Homeopathic Pharmacopoeia of the United States

All Native Remedies health products are especially formulated by experts in the field of natural health and are manufactures according to the highest pharmaceutical standards for maximum safety and effectiveness. For more information, visit us at www.nativeremedies.com

Distributed by
Native Remedies, LLC
6531 Park of Commerce Blvd
Suite 160
Boca Raton, FL 33487
Phone: +1.877.289.1235
International: 1.561.999.8857

No gluten, artificial flavors, or colorants added

STORAGE AND HANDLING

Tamper resistant for your protection. Use only if safety seal is intact